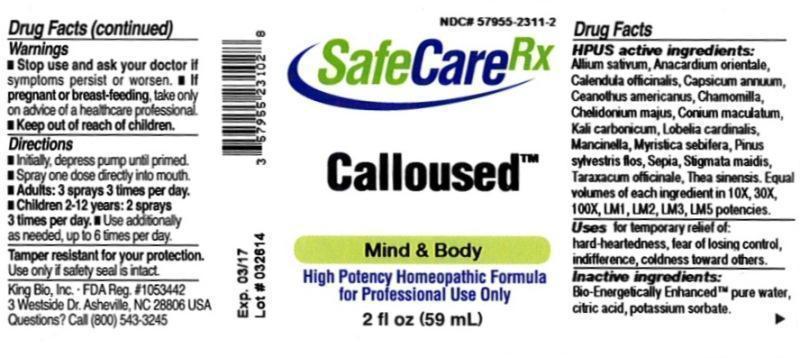 DRUG LABEL: Calloused
NDC: 57955-2311 | Form: LIQUID
Manufacturer: King Bio Inc.
Category: homeopathic | Type: HUMAN OTC DRUG LABEL
Date: 20140417

ACTIVE INGREDIENTS: GARLIC 10 [hp_X]/59 mL; SEMECARPUS ANACARDIUM JUICE 10 [hp_X]/59 mL; CALENDULA OFFICINALIS FLOWERING TOP 10 [hp_X]/59 mL; CAPSICUM 10 [hp_X]/59 mL; CEANOTHUS AMERICANUS LEAF 10 [hp_X]/59 mL; MATRICARIA RECUTITA 10 [hp_X]/59 mL; CHELIDONIUM MAJUS 10 [hp_X]/59 mL; CONIUM MACULATUM FLOWERING TOP 10 [hp_X]/59 mL; POTASSIUM CARBONATE 10 [hp_X]/59 mL; LOBELIA CARDINALIS 10 [hp_X]/59 mL; HIPPOMANE MANCINELLA FRUITING LEAFY TWIG 10 [hp_X]/59 mL; VIROLA SEBIFERA RESIN 10 [hp_X]/59 mL; PINUS SYLVESTRIS FLOWERING TOP 10 [hp_X]/59 mL; CORN SILK 10 [hp_X]/59 mL; SEPIA OFFICINALIS JUICE 10 [hp_X]/59 mL; TARAXACUM OFFICINALE 10 [hp_X]/59 mL; GREEN TEA LEAF 10 [hp_X]/59 mL
INACTIVE INGREDIENTS: WATER; CITRIC ACID MONOHYDRATE; POTASSIUM SORBATE

Calloused™

ACTIVE INGREDIENT

Drug Facts__________________________________________________________________________________________________________

HPUS activeingredients: Allium sativum, Anacardium orientale, Calendula officinalis, Capsicum annuum, Ceanothus americanus, Chamomilla, Chelidonium majus, Conium maculatum, Kali carbonicum, Lobelia cardinalis, Mancinella, Myristica sebifera, Pinus sylvestris, flos, Stigmata maidis, Sepia, Taraxacum officinale, Thea sinensis. Equal volumes of each ingredient in 10X, 30X, 100X, LM1, LM2, LM3, LM5 potencies.

INDICATIONS AND USAGE

Uses for temporary relief of: hard-heartedness, fear of losing control. indifference, coldness toward others.

Inactive Ingredients:

Bio-Energetically Enhanced™ pure water, citric acid and potassium sorbate.

Warnings

- Stop use and ask your doctor if symptoms persist or worsen.
- If pregnant or breast-feeding, take only on advice of a healthcare professional.

- Keep out of reach of children

Directions

- Initially, depress pump until primed.
- Spray one dose directly into mouth.
- Adults: 3 sprays 3 times per day.
- Children 2 - 12: 2 sprays 3 times per day.
- Use additionally as needed, up to 6 times per day.

OTHER SAFETY INFORMATION

Tamper resistant for your protection. Use only if safety seal is intact.

PURPOSE

Uses for temporary relief of:

- hard-heartedness
- fear of losing control
- indifference
- coldness toward others